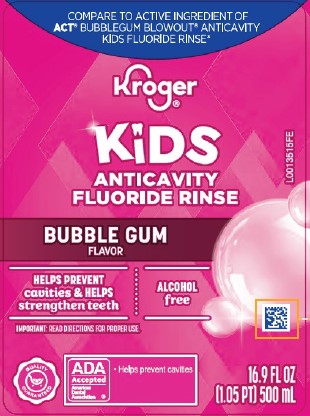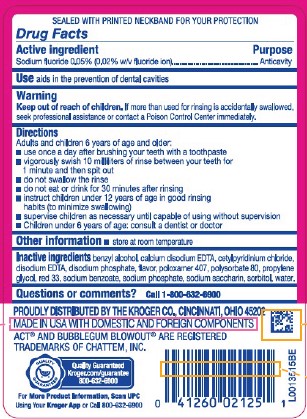 DRUG LABEL: Anticavity
NDC: 30142-004 | Form: RINSE
Manufacturer: The Kroger Co.
Category: otc | Type: HUMAN OTC DRUG LABEL
Date: 20260227

ACTIVE INGREDIENTS: SODIUM FLUORIDE 0.2 mg/1 mL
INACTIVE INGREDIENTS: BENZYL ALCOHOL; EDETATE CALCIUM DISODIUM ANHYDROUS; CETYLPYRIDINIUM CHLORIDE; EDETATE DISODIUM; SODIUM PHOSPHATE, DIBASIC, ANHYDROUS; POLOXAMER 407; POLYSORBATE 80; PROPYLENE GLYCOL; D&C RED NO. 33; SODIUM BENZOATE; SODIUM PHOSPHATE; SACCHARIN SODIUM; SORBITOL; WATER

Kroger 004.002/004AE
Anticavity Fluoride Rinse, Bubble Gum

Tamper Evident Statement

SEALED WITH PRINTED NECKBAND FOR YOUR PROTECTION

Active ingredient

Sodium fluoride 0.05% (0.02% w/v fluoride ion)

Purpose

Anticavity

Use

aids in the prevention of dental cavities

Warning

for this product

Keep out of reach of children.

If more than used for rinsing is accidentally swallowed, seek professional assistance or contact a Poison Control Center immediately.

Directions

Adults and children 6 years of age and older:

- use once a day after brushing your teeth with toothpaste
- vigorously swish 10 milliliters of rinse between your teeth for 1 minute and then spit out
- do not swallow the rinse
- do not eat or drink for 30 minutes after rinsing
- instruct children under 12 years of age in good rinsing habits (to minimize swallowing)
- supervise children as necessary until capable of using without supervision
- Children under 6 years of age: consult a dentist or doctor

Other information

- store at room temperature

Inactive ingredients

benzyl alcohol, calcium disodium EDTA, cetylpridinium chloride, disodium EDTA, disodium phosphate, flavor, poloxamer 407, polysorbate 80, propylene glycol, red 33, sodium benzoate, sodium phosphate, sodium saccharin, sorbitol, water

Questions or comments?

Call 1-800-632-6900

Disclaimer

ACT® AND BUBBLEGUM BLOWOUT®ARE REGISTERED TRADEMARKS OF CHATTEM, INC.

Adverse reaction

PROUDLY DISTRIBUTED BY THE KROGER CO., CINCINNATI, OH 45202

MADE IN USA WITH DOMESTIC AND FOREIGN COMPONENTS

QUALITY GUARANTEED

Kroger.com/guarantee

800-632-6900

For more product information, scan UPC using your Kroger App or call 800-632-6900

Principal display panel

Compare to the active ingredient of ACT® Bubblegun Blowout®Anticavity Kids Fluoride Rinse*

Kroger®

Kids

Anticavity

Fluoride Rinse

Bubble Gum Flavor

Helps Prevent cavities & Helps strengthen teeth

Alcohol free

IMPORTANT: Read directions for proper use.

QUALITY GUARANTEED

ADA Accepted

American Dental Association

- Helps prevent cavities

16.9 FL OZ (1.05 PT) 500 mL